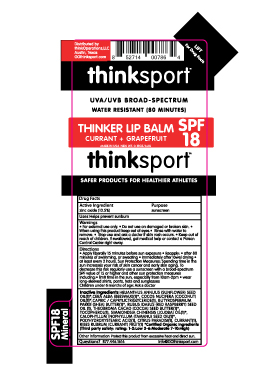 DRUG LABEL: Thinksport 
NDC: 60781-3001 | Form: STICK
Manufacturer: thinkOperations,LLC
Category: otc | Type: HUMAN OTC DRUG LABEL
Date: 20200123

ACTIVE INGREDIENTS: ZINC OXIDE 105 ug/1 g
INACTIVE INGREDIENTS: TRICAPRIN; COCONUT OIL; TOCOPHEROL; SUNFLOWER OIL; RED CURRANT; TAMANU OIL; SHEA BUTTER; RASPBERRY SEED OIL; COCOA BUTTER; JOJOBA OIL; GRAPEFRUIT; STEARIC ACID; WHITE WAX

thinksportTM
THINKER LIP BALM
CURRANT + GRAPEFRUIT

Active Ingredient

zinc oxide (10.5%)

Purpose

sunscreen

Uses

Helps prevent sunburn

Warnings

For external use only.

Do not use on damaged or broken skin.

When using

When using this product keep out of eyes. Rinse with water to remove.

Stop use and ask a doctor if skin rash occurs.

Keep out of reach of children. If swallowed, get medical help or contact a Poison Control Center right away.

Directions

• Apply liberally 15 minutes before sun exposure

• Reapply:

• after 80 minutes of swimming, or sweating

• immediately after towel drying

• at least every 2 hours

Sun Protection Measures:

Spending time in the sun increases your risk of skin cancer and early skin aging. To decrease this risk regularly use a sunscreen with a broad-spectrum SPF value of 15 or higher and other sun protection measures including:

• limit time in the sun, especially from 10am-2pm

• wear long-sleeved shirts, pants, hats and sunglasses

Children under 6 months of age: Ask a doctor

Inactive Ingredients

HELIANTHUS ANNUUS (SUNFLOWER) SEED OIL*(1),CERA ALBA (BEESWAX)(1)*, COCOS NUCIFERA (COCONUT) OIL(1)*,CAPRIC / CAPRYLICTRIGLYCERIDE(1),BUTYROSPERMUM PARKII (SHEA) BUTTER*(1),VITIS VINIFERA (GRAPE)SEED OIL(1),TOCOPHEROL(1),CITRUS PARADISI(1), CURRANT (1),RIBES RUBRUM (CURRANT) FRUIT(1)

*Certified Organic Ingredients (Third party safety rating: 1-2:Low 3-6:Moderate 7-10:High)

Other information

Protect this product from excessive heat and direct sun.

Questions?

Questions? 877.446.1616 info@GOthinksport.com

Distributed by

thinkOperations, LLC

Austin, Texas

GOthinksport.com

UVA/UVB BROAD-SPECTRUM

WATER RESISTANT (80 MINUTES)

THINKER LIP BALM

CURRANT + GRAPEFRUIT

SPF 18

MADE IN USA

NET WT. 0.15 OZ/ 4.2G